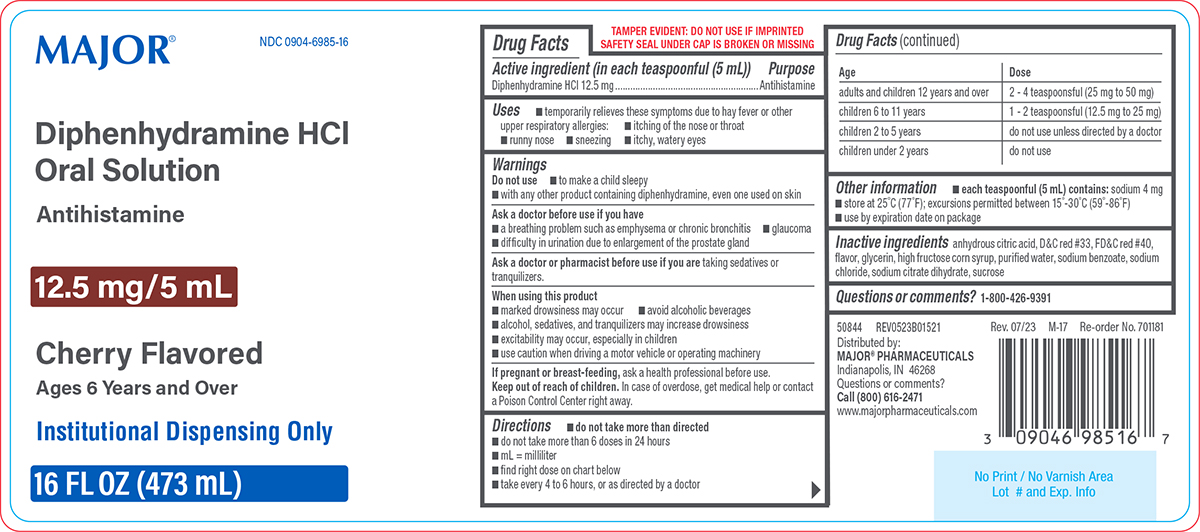 DRUG LABEL: Diphenhydramine HCl
NDC: 0904-6985 | Form: SOLUTION
Manufacturer: Major Pharmaceuticals
Category: otc | Type: HUMAN OTC DRUG LABEL
Date: 20260209

ACTIVE INGREDIENTS: DIPHENHYDRAMINE HYDROCHLORIDE 12.5 mg/5 mL
INACTIVE INGREDIENTS: ANHYDROUS CITRIC ACID; D&C RED NO. 33; FD&C RED NO. 40; GLYCERIN; HIGH FRUCTOSE CORN SYRUP; WATER; SODIUM BENZOATE; SODIUM CHLORIDE; TRISODIUM CITRATE DIHYDRATE; SUCROSE

Major 44-015 Delisted

Active ingredient (in each teaspoonful (5 mL))

Diphenhydramine HCl 12.5 mg

Purpose

Antihistamine

Uses

- temporarily relieves these symptoms due to hay fever or other upper respiratory allergies:
  - itching of the nose or throat
  - runny nose
  - sneezing
  - itchy, watery eyes

Warnings

Do not use

- to make a child sleepy
- with any other product containing diphenhydramine, even one used on skin

Ask a doctor before use if you have

- a breathing problem such as emphysema or chronic bronchitis
- glaucoma
- difficulty in urination due to enlargement of the prostate gland

Ask a doctor or pharmacist before use if you are

taking sedatives or tranquilizers.

When using this product

- marked drowsiness may occur
- avoid alcoholic beverages
- alcohol, sedatives, and tranquilizers may increase drowsiness
- excitability may occur, especially in children
- use caution when driving a motor vehicle or operating machinery

If pregnant or breast-feeding,

ask a health professional before use.

Keep out of reach of children.

In case of overdose, get medical help or contact a Poison Control Center right away.

Directions

- do not take more than directed
- do not take more than 6 doses in 24 hours
- mL = milliliter
- find right dose on chart below
- take every 4 to 6 hours, or as directed by a doctor

Age | Dose
adults and children 12 years and over | 2 - 4 teaspoonsful (25 mg to 50 mg)
children 6 to 11 years | 1 - 2 teaspoonsful (12.5 mg to 25 mg)
children 2 to 5 years | do not use unless directed by a doctor
children under 2 years | do not use

Other information

- each teaspoonful (5 mL) contains: sodium 4 mg
- store at 25°C (77°F); excursions permitted between 15°-30°C (59°-86°F)
- use by expiration date on package

Inactive ingredients

anhydrous citric acid, D&C red #33, FD&C red #40, flavor, glycerin, high fructose corn syrup, purified water, sodium benzoate, sodium chloride, sodium citrate dihydrate, sucrose

Questions or comments?

1-800-426-9391

Principal display panel

MAJOR®

NDC 0904-6985-16

Diphenhydramine HCl
Oral Solution

Antihistamine

12.5 mg/5 mL

Cherry Flavored

Ages 6 Years and Over

Institutional Dispensing Only

16 FL OZ (473 mL)

TAMPER EVIDENT: DO NOT USE IF IMPRINTED
SAFETY SEAL UNDER CAP IS BROKEN OR MISSING

50844 REV0523B01521
Distributed by:
MAJOR® PHARMACEUTICALS
Indianapolis, IN 46268
Questions or comments?
Call (800) 616-2471
www.majorpharmaceuticals.com

Rev. 07/23 M-17 Re-order No. 701181

Major 44-015